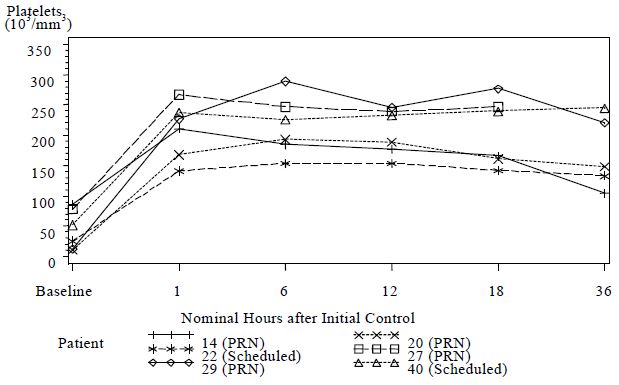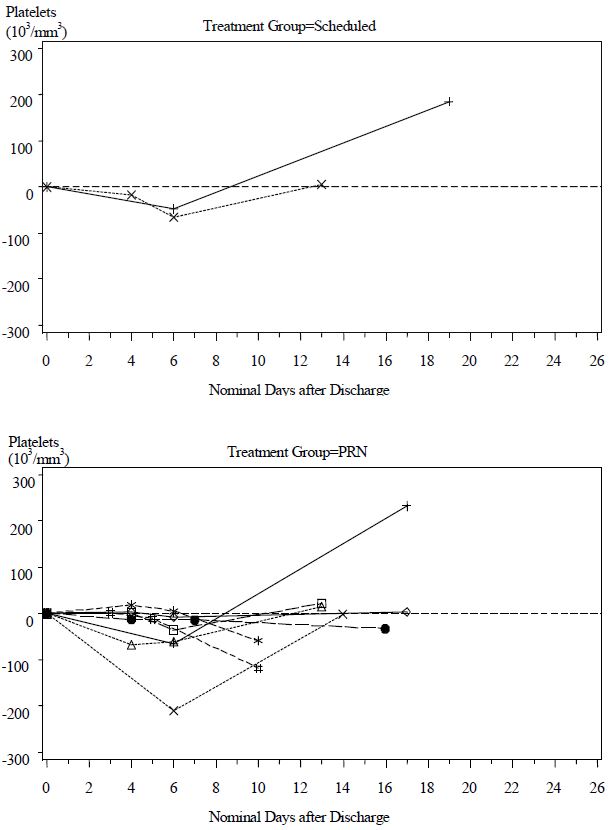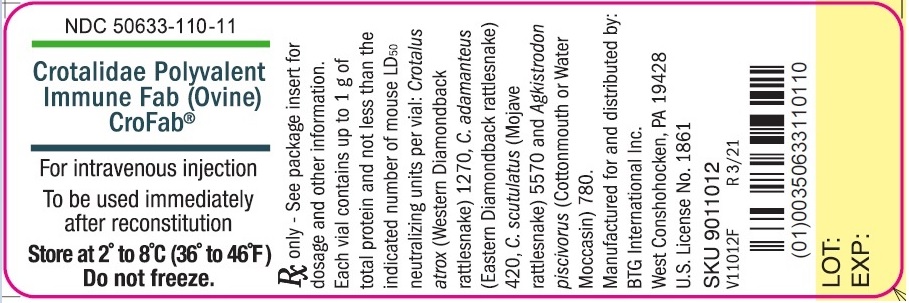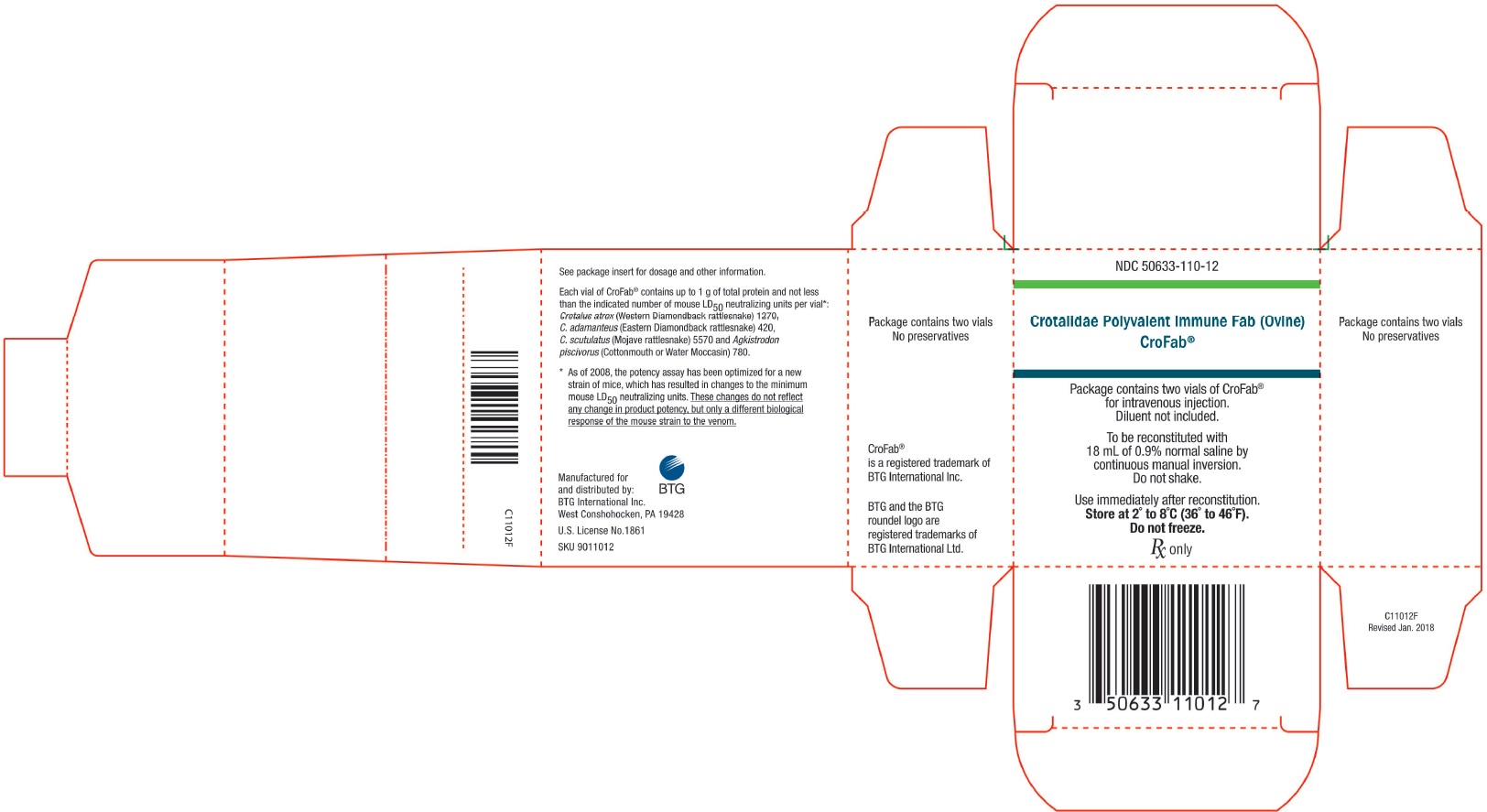 DRUG LABEL: CroFab
NDC: 50633-110 | Form: INJECTION, POWDER, LYOPHILIZED, FOR SOLUTION
Manufacturer: BTG International Inc.
Category: other | Type: PLASMA DERIVATIVE
Date: 20241118

ACTIVE INGREDIENTS: CROTALUS ATROX IMMUNE FAB ANTIVENIN (OVINE) 1 g/1 1; AGKISTRODON PISCIVORUS IMMUNE FAB ANTIVENIN (OVINE) 1 g/1 1; CROTALUS SCUTULATUS IMMUNE FAB ANTIVENIN (OVINE) 1 g/1 1; CROTALUS ADAMANTEUS IMMUNE FAB ANTIVENIN (OVINE) 1 g/1 1
INACTIVE INGREDIENTS: SODIUM PHOSPHATE, DIBASIC, ANHYDROUS; SODIUM CHLORIDE

HIGHLIGHTS OF PRESCRIBING INFORMATION

These highlights do not include all the information needed to use CROFAB safely and effectively. See full prescribing information for CROFAB.
CROFAB® crotalidae polyvalent immune fab (ovine)
Lyophilized Powder for Solution for Intravenous Injection
Initial U.S. Approval: 2000

RECENT MAJOR CHANGES

Dosage and Administration, Preparation and Administration (2.2) | 01/2018
Dosage Forms and Strengths (3) | 01/2018
Warning and Precautions, Mercury Toxicity (5.3) - REMOVED | 01/2018
Use in Specific Population (8) | 01/2018
Description (11) | 01/2018

1 INDICATIONS AND USAGE

CROFAB is a sheep-derived antivenin indicated for the management of adult and pediatric patients with North American crotalid envenomation. (1)

2 DOSAGE AND ADMINISTRATION

For intravenous use only

- Initiate administration as soon as possible after snake bite in patients who develop signs of envenomation (e.g. local injury, coagulation abnormality or systemic signs of envenomation)
- Dose: (2.1)
  - Recommended initial dose is between 4 and 6 vials
  - Observe patient for up to one hour after the initial dose and give an additional 4-6 vial dose as needed to gain initial control of envenomation
  - After initial control is established, administer additional 2-vial doses every 6 hours for 18 hours (total of 3 doses)
- Preparation and Administration: (2.2)
  - Reconstitute each vial of CROFAB with 18 mL of 0.9% Sodium Chloride and mix by continuous manual inversion at the rate of one to two inversions per second until no solid material is visible in the vial (contents will remain opalescent)
  - Do not shake as this can cause foaming
  - Further dilute the entire dose with 0.9% Sodium Chloride to a total volume of 250 mL
  - Infuse each dose intravenously over at least 1 hour

3 DOSAGE FORMS AND STRENGTHS

CROFAB is available as lyophilized powder. Each vial contains up to 1 gram of total protein and not less than the indicated number of mouse LD50 neutralizing units:

Snake Species Used for Antivenin Component | Minimum mouse LD50Units per vial
C. atrox (Western Diamondback rattlesnake) | 1270
C. adamanteus (Eastern Diamondback rattlesnake) | 420
C. scutulatus (Mojave rattlesnake) | 5570
A. piscivorus (Cottonmouth or Water Moccasin) | 780

4 CONTRAINDICATIONS

Do not administer CROFAB to patients with a known history of hypersensitivity to any of its components, or to papaya or papain unless the benefits outweigh the risks and appropriate management for anaphylactic reactions is readily available. (4)

5 WARNINGS AND PRECAUTIONS

- Monitor patients for recurrent coagulopathy for one week or longer following treatment of the bite (5.1)
- Hypersensitivity reactions, including anaphylaxis, may occur (5.2)
- Patients allergic to papain, chymopapain, papaya extracts, or bromelain (pineapple enzyme), may react to CROFAB (5.2)

6 ADVERSE REACTIONS

Most common adverse reactions (incidence ≥5% of subjects): urticaria, rash, nausea and pruritus. Allergic reaction (severe hives and a severe rash and pruritus) has occurred following treatment.

Recurrent coagulopathy due to envenomation and requiring additional treatment may occur. (5.1)

To report SUSPECTED ADVERSE REACTIONS, contact 1-877-377-3784 or FDA at 1-800-FDA-1088 or www.fda.gov/medwatch.

FULL PRESCRIBING INFORMATION

1 INDICATIONS AND USAGE

CROFAB is indicated for the management of adult and pediatric patients with North American crotalid envenomation. The term crotalid is used to describe the Crotalinae subfamily (formerly known as Crotalidae) of venomous snakes which includes rattlesnakes, copperheads and cottonmouths/water moccasins.

2 DOSAGE AND ADMINISTRATION

For intravenous use only

2.1 Dose

- Administer CROFAB as soon as possible in patients who develop any signs of envenomation (e.g., local injury, coagulation abnormality or systemic signs of envenomation) to prevent clinical deterioration. CROFAB was shown in clinical studies to be effective when given within 6 hours of snakebite.
- Antivenin dosage requirements are contingent upon an individual patient’s response. Based on clinical experience with CROFAB, the recommended initial dose is 4 to 6 vials; however, the starting dose may vary from a minimum of 4 vials to a maximum of 12 vials based on clinical judgment and severity of envenomation [3].
- Observe the patient for up to 1 hour following completion of the first dose to determine if initial control of envenomation has been achieved. Initial control is achieved when local signs of envenomation are arrested (leading edge of local injury is not progressing), systemic symptoms are resolved and coagulation parameters have normalized or are trending toward normal. If initial control is not achieved by the first dose, an additional dose of 4 to 6 vials should be administered repeatedly until initial control of the envenomation syndrome has been achieved.
- Once initial control has been achieved, additional 2-vial doses of CROFAB every 6 hours for up to 18 hours (3 doses) are recommended. Optimal dosing following the 18-hour scheduled dose of CROFAB has not been determined. Additional 2-vial doses may be administered as deemed necessary by the treating physician, based on the patient’s clinical course.
- Infusion reactions, such as fever, low back pain, wheezing and nausea, may be related to the rate of infusion and can be controlled by decreasing the rate of administration of the solution [12]. Poison control centers are a helpful resource for individual treatment advice.

2.2 Preparation and Administration

- Parenteral drug products should be inspected visually for particulate matter and discoloration prior to administration, whenever solution and container permit.
- Reconstitute each vial of CROFAB with 18 mL of 0.9% Sodium Chloride (diluent not included) and mix by continuous manual inversion at the rate of one to two inversions per second until no solid material is visible in the vial (the fully reconstituted product will still be opalescent). Do not shake as this can cause foaming. Further dilute the contents of all of the reconstituted vials to a total volume of 250 mL with 0.9% Sodium Chloride and mix by gently swirling.
- Use the reconstituted and diluted product within 4 hours.
- Infuse the dose intravenously over 60 minutes. However, the infusion should proceed slowly over the first 10 minutes at a 25- 50 mL/hour rate with careful observation for any allergic reaction. If no such reaction occurs, the infusion rate may be increased to the full 250 mL/hour rate until completion. Close patient monitoring is necessary.

3 DOSAGE FORMS AND STRENGTHS

CROFAB is available as a sterile, nonpyrogenic, purified, lyophilized powder. Each vial contains up to 1 gram of total protein and not less than the indicated number of mouse LD50 neutralizing units*:

Snake Species Used for Antivenin Component | Minimum mouse LD50 Units per vial
C. atrox (Western Diamondback rattlesnake) | 1270
C. adamanteus (Eastern Diamondback rattlesnake) | 420
C. scutulatus (Mojave rattlesnake) | 5570
A. piscivorus (Cottonmouth or Water Moccasin) | 780
* As of 2008, the potency assay has been optimized for a new strain of mice, which has resulted in changes to the minimum mouse LD50 neutralizing units. These changes do not reflect any change in product potency, but only a different biological response of the mouse strain to the venom.

4 CONTRAINDICATIONS

Do not administer CROFAB to patients with a known history of hypersensitivity to papaya or papain unless the benefits outweigh the risks and appropriate management for anaphylactic reactions is readily available.

5 WARNINGS AND PRECAUTIONS

5.1 Coagulopathy

Coagulopathy is a complication noted in many victims of crotalid envenomation that arises due to the ability of the snake venom to interfere with the blood coagulation cascad [5, 9, 10], and is seen more frequently in severely envenomated patients.

In clinical trials with CROFAB, recurrent coagulopathy (the return of a coagulation abnormality after it has been successfully treated with antivenin), characterized by decreased fibrinogen, decreased platelets and elevated prothrombin time, occurred in approximately half of patients studied. The clinical significance of these recurrent abnormalities is not known; however, one systematic review of the literature showed that medically significant bleeding following treatment of Crotaline snake envenomation is uncommon, occurring with an estimated frequency of 0.5% [13]. Recurrent coagulation abnormalities were observed only in patients who experienced coagulation abnormalities during their initial hospitalization, although coagulopathy can initially appear at any time before, during or after treatment. Optimal dosing to completely prevent recurrent coagulopathy has not been determined. Because CROFAB has a shorter persistence in the blood than the snake venoms that can leak from depot sites over a prolonged period of time, repeat dosing to prevent or treat such recurrence may be necessary [see Dosage and Administration (2)].

Recurrent coagulopathy may persist for 1 to 2 weeks or more. Patients who experience coagulopathy due to snakebite during hospitalization for initial treatment should be monitored for signs and symptoms of recurrent coagulopathy for up to 1 week or longer at the physician’s discretion. During this period, the physician should carefully assess the need for re-treatment with CROFAB and use of any type of anticoagulant or anti-platelet drug.

Because snake envenomation can cause coagulation abnormalities, the following conditions, which are also associated with coagulation defects, should be considered: cancer, collagen disease, congestive heart failure, diarrhea, elevated temperature, hepatic disorders, hyperthyroidism, poor nutritional state, steatorrhea, vitamin K deficiency.

5.2 Hypersensitivity Reactions

Severe hypersensitivity reactions may occur with CROFAB. In case of acute hypersensitivity reactions, including anaphylaxis and anaphylactoid reactions, discontinue infusion and institute appropriate emergency treatment.

CROFAB contains purified immunoglobulin fragments from the blood of sheep that have been immunized with snake venoms [see Description (11)]. Injection of heterologous animal proteins can cause severe acute and delayed hypersensitivity reactions (late serum reaction or serum sickness) and a possible febrile response to immune complexes formed by animal antibodies and neutralized venom components [11].

Papain is used to cleave antibodies into fragments during the processing of CROFAB, and trace amounts of papain or inactivated papain residues may be present. Patients allergic to papain, chymopapain, other papaya extracts, or the pineapple enzyme bromelain may also have an allergic reaction to CROFAB. Some dust mite allergens and some latex allergens share antigenic structures with papain and patients with these allergies may be allergic to papain [7, 8].

Use the following precautions to manage hypersensitivity reactions:

- Emergency medical care (e.g., epinephrine, intravenous antihistamines and/or albuterol) should be readily available.
- Carefully monitor patients for signs and symptoms of an acute allergic reaction (e.g., urticaria, pruritus, erythema, angioedema, bronchospasm with wheezing or cough, stridor, laryngeal edema, hypotension, tachycardia).
- Follow-up all patients for signs and symptoms of delayed allergic reactions or serum sickness (e.g., rash, fever, myalgia, arthralgia).

Patients who receive a course of treatment with a foreign protein such as CROFAB may become sensitized to it. Therefore, caution should be used when administering a repeat course of treatment with CROFAB for a subsequent envenomation episode.

Skin testing has not been used in clinical trials of CROFAB and is not required.

6 ADVERSE REACTIONS

Most common adverse reactions (incidence ≥5% of subjects) were urticaria, rash, nausea, pruritus and back pain.

The following clinically significant adverse reactions are described elsewhere in the labeling:

- Hypersensitivity Reactions [see Warnings and Precautions (5.2)]

6.1 Clinical Trials Experience

Because clinical trials are conducted under widely varying conditions, adverse reaction rates observed in the clinical trials of a drug cannot be directly compared to rates in the clinical trials of another drug and may not reflect the rates observed in clinical practice.

The safety of CROFAB was evaluated in 289 patients who received CROFAB for crotalid envenomation. Forty-two patients were from two prospective clinical trials in patients who experienced mild to moderate crotalid envenomation; 247 patients were from a retrospective study in patients who experienced mild, moderate or severe envenomation. There also were safety information extracted from literature review of publications on CROFAB that contained patient exposure data.

Premarketing Prospective Clinical Trials

A total 42 patients received CROFAB for treatment of mild to moderate crotalid envenomation in two clinical studies. The patients were aged 11 to 76 years, and 34 were male and 8 were female. Nineteen patients experienced an adverse reaction for a total of 26 adverse reactions. Adverse reactions involving the skin and appendages (primarily rash, urticaria, and pruritus) were reported in 12 of the 42 patients (see Table 1). One patient discontinued CROFAB therapy due to an allergic reaction.

Of the 19 patients who experienced adverse reactions, 3 patients experienced severe or serious adverse reactions.

- 1 patient who experienced a serious adverse reaction had recurrent coagulopathy due to envenomation, which required re-hospitalization and additional antivenin administration. This patient eventually made a complete recovery.
- 2 patients had severe adverse reactions that consisted of 1 patient who developed severe urticaria following treatment and 1 patient who developed a severe rash and pruritus several days following treatment. Both patients recovered following treatment with antihistamines and prednisone.

Table 1 Incidence of Adverse Reactions by Body System in Premarketing Clinical Trials
Adverse Reaction | n=42 Number of Reactions
Body as a Whole
Back pain | 2
Allergic reaction† | 1
Serum sickness | 1
Skin and Appendages
Urticaria | 7
Rash | 3
Pruritus | 2
Subcutaneous nodule | 1
Respiratory System
Cough | 1
Digestive System
Nausea | 3
Anorexia | 1
Hematologic/Lymphatic
Coagulation disorder | 1
Ecchymosis | 1
Musculoskeletal
Myalgia | 1
Nervous System
Nervousness | 1
† Allergic reaction consisted of urticaria, dyspnea and wheezing in 1 patient.

Six of 42 patients experienced an adverse reaction associated with an early serum reaction and 4 experienced an adverse reaction associated with a late serum reaction. Two additional patients were considered to have experienced a late serum reaction by the investigator, although no associated adverse reaction was reported. Serum reactions are defined as reactions associated with CROFAB infusion. They consisted mainly of urticaria and rash, and all patients recovered without sequelae. Table 2 lists the incidence of early and late serum reactions. There were 7 events classified as early serum reactions and 5 events classified as late serum reactions; none was serious.

Table 2 Incidence of Early and Late Serum Reactions in Premarketing Clinical Trials
 | n=42 Number of Events
Early Serum Reactions
Urticaria | 5
Cough | 1
Allergic reaction** | 1
Late Serum Reactions
Rash | 2
Pruritus | 1
Urticaria | 1
Serum sickness† | 1
** Allergic reaction consisted of urticaria, dyspnea and wheezing in 1 patient.
† Serum sickness consisted of severe rash and pruritus in 1 patient.

Postmarketing Retrospective Study

This was a retrospective study of data collected from postmarketing use of CROFAB to compare treatment and outcome characteristics between patients with severe envenomation to those with mild to moderate envenomation. A total of 247 patients received CROFAB for treatment of mild, moderate or severe crotalid envenomation. The patients were aged 1 to 91 years, and 206 were male and 41 were female. Of the 247 patients, 209 were classified as mild/moderate (n=181) or severe (n=28), while 38 patients did not have enough data to calculate an initial severity score.

There were a total of 36 immediate adverse drug reactions reported in 15 patients (6.1%, n = 247).

- There were 11 immediate serious adverse events related to CROFAB administration reported in four patients. The events included two episodes each of hypotension and tongue swelling, and one episode each of chest discomfort, angioedema, bronchospasm, wheezing, tracheal edema, dyspnea, and lip swelling.
- There were 22 immediate non-serious adverse events related to CROFAB administration reported in 12 patients. The events included four episodes each of rash and pruritus, three episodes of urticaria and one episode each of tachycardia, tachypnea, erythema, swelling, hyperhidrosis, dizziness, headache, musculoskeletal chest pain, chills, feeling cold and nervousness.

Delayed hypersensitivity reactions were reported for two patients. In one patient, symptoms described as hives, itching and epigastric pressure occurred 6 days post-dosing and were not serious. In the second patient, symptoms were not described in the medical records and therefore were not captured in this study.

Recurrent coagulopathy developed in 5 severely envenomated patients and in 6 mild/moderate envenomated patients. In addition, 7 mild/moderate patients experienced delayed-onset coagulopathy. One severely envenomated patient with recurrent coagulopathy experienced medically significant bleeding.

Additional Published Clinical Studies Experience

From a literature review of nine publications on CROFAB that contained patient exposure data, 15 of 313 (4.8%) patients receiving CROFAB experienced acute hypersensitivity reactions. The most common signs and symptoms associated with these reactions were rash (10 patients) and wheezing (3 patients). Most reactions were mild, resolved after antihistamine therapy, and did not require discontinuation of antivenom therapy. No patient developed a life-threatening hypersensitivity reaction, required intubation, suffered lasting ill-effect or died as a result of CROFAB administration.

Follow up data (minimum of six days after treatment) were available in 94 of the 313 patients. Delayed hypersensitivity reactions were reported in 10 cases. The most common signs and symptoms of delayed hypersensitivity were rash (9 patients) and fever (3 patients). Most were mild and treated with antihistamines and steroids.

6.2 Postmarketing Experience

The following additional adverse reactions have been identified during the post approval use of CROFAB. Because these reactions are reported voluntarily from a population of uncertain size, it is not always possible to reliably estimate their frequency or establish a causal relationship to product exposure:

- Delayed allergic reaction manifested by fever, pruritis and/or rash
- Delayed or recurrent coagulopathy or thrombocytopenia
- Failure to achieve initial control
- Recurrent swelling refractory to treatment
- Thrombocytopenia refractory to treatment
- Prolonged hospitalization
- Bleeding
- Tremor
- Treatment failure resulting in death

8 USE IN SPECIFIC POPULATIONS

8.1 Pregnancy

Risk Summary
Animal reproduction studies have not been conducted with CROFAB. It is also not known whether CROFAB can cause fetal harm when administered to a pregnant woman or can affect reproduction capacity. CROFAB should be given to a pregnant woman only if clearly needed. In the U.S. general population, the estimated background risk of major birth defects and miscarriage in clinically recognized pregnancies is 2-4% and 15-20%, respectively.

8.2 Lactation

Risk Summary
It is not known whether CROFAB is excreted in human breast milk. Because many drugs are excreted in human milk, caution should be exercised when CROFAB is administered to a nursing woman.

8.4 Pediatric Use

Thirty-two percent (78/247) of patients studied in a post-marketing retrospective study of CROFAB were 16 years of age or younger (median 8.5 years [range 1 to 16 years]). Initial control of envenomation was achieved in 64/72 (89%) of pediatric patients, which was similar to the initial control rate in adults (103/128, 80%). Changes in severity score, recurrence and incidence adverse reactions were similar between pediatric and adult patients, indicating safety and efficacy in the pediatric population are comparable to that in adults. Limited published clinical experience has not shown that a dosage adjustment for age should be made [14, 15].

8.5 Geriatric Use

Five percent (13/247) of patients studied in a post-marketing retrospective study of CROFAB were over 65 years of age (median 72 years [range 67 to 91 years]). The efficacy and safety of CROFAB in the geriatric population appears comparable to the overall population.

11 DESCRIPTION

CROFAB [Crotalidae Polyvalent Immune Fab (Ovine)] is a sterile, nonpyrogenic, purified, lyophilized preparation of ovine Fab (monovalent) immunoglobulin fragments obtained from the blood of healthy sheep flocks immunized with one of the following North American snake venoms: Crotalus atrox (Western Diamondback rattlesnake), Crotalus adamanteus (Eastern Diamondback rattlesnake), Crotalus scutulatus (Mojave rattlesnake), and Agkistrodon piscivorus (Cottonmouth or Water Moccasin). To obtain the final antivenin product, the four different monospecific antivenins are mixed. Each monospecific antivenin is prepared by fractionating the immunoglobulin from the ovine serum, digesting it with papain, and isolating the venom specific Fab fragments on ion exchange and affinity chromatography columns.

CROFAB is standardized by its ability to neutralize the lethal action of each of the four venom immunogens following intravenous injection in mice. The potency of the product will vary from batch to batch; however, a minimum number of mouse LD50 neutralizing units against each of the four venoms is included in every vial of final product, as shown in Table 3.

Table 3 Minimum Mouse LD50 Neutralizing Units^1 for Each Venom Component
Venom | Minimum Potency per Vial of CROFAB^2
Crotalus atrox | ≥ 1270
Crotalus adamanteus | ≥ 420
Crotalus scutulatus | ≥ 5570
Agkistrodon piscivorus | ≥ 780
^1 One neutralizing unit is determined as the amount of the mixed monospecific Fab proteins necessary to neutralize one LD50 of each of the four venoms, where the LD50 is the amount of venom that would be lethal in 50% of mice.
^2 As of 2008, the potency assay has been optimized for a new strain of mice, which has resulted in changes to the minimum mouse LD50 neutralizing units. These changes do not reflect any change in product potency, but only a different biological response of the mouse strain to the venom.

Each vial of CROFAB contains up to 1 gram of total protein and sodium phosphate buffer consisting of dibasic sodium phosphate USP and sodium chloride USP. The product is intended for intravenous administration after reconstitution with 18 mL of 0.9% Sodium Chloride.

12 CLINICAL PHARMACOLOGY

12.1 Mechanism of Action

CROFAB is a venom-specific Fab fragment of immunoglobulin G (IgG) that works by binding and neutralizing venom toxins, facilitating their redistribution away from target tissues and their elimination from the body.

12.3 Pharmacokinetics

A limited number of samples were collected from three patients in the pharmacokinetic study of CROFAB. Based on these data, estimates of elimination half-life were made. The elimination half life for total Fab ranged from approximately 12 to 23 hours. These limited pharmacokinetic estimates of half-life are augmented by data obtained with an analogous ovine Fab product produced by BTG International Inc. using a similar production process. In that study, 8 healthy subjects were given 1 mg of intravenous digoxin followed by an approximately equimolar neutralizing dose of 76 mg of digoxin immune Fab (ovine). Total Fab was shown to have a volume of distribution of 0.3 L/kg, a systemic clearance of 32 mL/min (approximately 0.4 mL/min/kg) and an elimination half-life of approximately 15 hours.

13 NONCLINICAL TOXICOLOGY

13.2 Animal Toxicology and/or Pharmacology

CROFAB was effective in neutralizing the venoms of 10 clinically important North American crotalid snakes in a murine lethality model (see Table 4) [1]. In addition, preliminary data from experiments in mice using whole IgG from the sheep immunized for CROFAB production suggest that CROFAB might possess antigenic cross-reactivity against the venoms of some Middle Eastern and North African snakes; however, there are no clinical data available to confirm these findings.

Table 4 Average ED50 Values for CROFAB in Mice
Study Objective & Design | Endpoint Measured | Major Findings and Conclusions
To determine the cross-neutralizing ability of CROFAB to protect mice from the lethal effects of venom from clinically important species. Separate groups of mice were injected with increasing doses of CROFAB pre-mixed with two LD50 of each venom tested. | ED50 for each venom | (Note: Lower numbers represent increased potency against venoms listed) Challenge Venom ED50 (mg antivenin/mg venom) C. atrox 3 C. adamanteus 18 C. scutulatus 8 A. piscivorus 4 C. h. atricaudatus 11 C. v. helleri 6 C. m. molossus 5 A. c. contortrix 8 S. m. barbouri 12 C. h. horridus 6
 |  | Based on data from studies in mice, CROFAB has relatively good cross-protection against venoms not used in the immunization of flocks used to produce it. For C. v. helleri and C. m. molossus, higher doses may be required based on historical data.

14 CLINICAL STUDIES

The safety and efficacy of CROFAB in crotalid envenomation were evaluated in two premarketing prospective and one postmarketing retrospective studies. The prospective studies evaluated patients suffering from minimal to moderate North American crotalid envenomation. The postmarketing study evaluated patients suffering from mild, moderate or severe envenomation. The definition of minimal, moderate, and severe envenomation in clinical studies of CROFAB is provided in Table 5.

Table 5 Definition of Minimal, Moderate, and Severe Crotalid Envenomation
Envenomation Severity | Definition
Minimal | Swelling, pain, and ecchymosis limited to the immediate bite site; Systemic signs and symptoms absent; Coagulation parameters normal with no clinical evidence of bleeding
Moderate | Swelling, pain, and ecchymosis involving less than a full extremity or, if bite was sustained on the trunk, head or neck, extending less than 50 cm; Systemic signs and symptoms may be present but not life threatening, including but not limited to nausea, vomiting, oral paresthesia or unusual tastes, mild hypotension (systolic blood pressure >90 mmHg), mild tachycardia (heart rate <150), and tachypnea Coagulation parameters may be abnormal, but no clinical evidence of bleeding present. (Minor hematuria, gum bleeding and nosebleeds are allowed if they are not considered severe in the investigator’s judgment)
Severe | Swelling, pain, and ecchymosis involving more than an entire extremity or threatening the airway Systemic signs and symptoms are markedly abnormal, including severe alteration of mental status, severe hypotension, severe tachycardia, tachypnea, or respiratory insufficiency Coagulation parameters are abnormal, with serious bleeding or severe threat of bleeding

Premarketing Prospective Studies

Two premarketing prospectively defined, open label, multi-center trials were conducted in otherwise healthy patients 11 years of age or older who had experienced minimal or moderate North American crotalid envenomation that showed evidence of progression. Progression was defined as the worsening of any evaluation parameter used in the grading of an envenomation: local injury, laboratory abnormality or symptoms and signs attributable to crotalid snake venom poisoning. Both clinical trials excluded patients with Copperhead envenomation.

Efficacy was determined using a Snakebite Severity Score (SSS) [2] (referred to as the efficacy score or ES) and an investigator’s clinical assessment (ICA) of efficacy. The SSS is a tool used to measure the severity of envenomation based on six body categories: local wound (e.g., pain, swelling and ecchymosis), pulmonary, cardiovascular, gastrointestinal, hematological and nervous system effects. A higher score indicates worse symptoms.. CROFAB was required to prevent an increase in the ES in order to demonstrate efficacy.

The ICA was based on the investigator’s clinical judgment as to whether the patient had a:

- Clinical response (pre-treatment signs and symptoms of envenomation were arrested or improved after treatment)
- Partial response (signs and symptoms of envenomation worsened, but at a slower rate than expected after treatment)
- Non-response (the patient’s condition was not favorably affected by the treatment)

Safety was assessed during CROFAB infusion by monitoring for early allergic events, such as anaphylaxis and early serum reactions, and late events, such as late serum reactions [see Adverse Reactions (6.1)]

In clinical study 1, 11 patients received an intravenous dose of 4 vials of CROFAB over 60 minutes. An additional 4-vial dose of CROFAB was administered after completion of the first CROFAB infusion, if deemed necessary by the investigator. At the 1-hour assessment, 10 out of 11 patients had no change or a decrease in their ES. Ten of 11 patients were also judged to have a clinical response by the ICA. After initial clinical response, two patients demonstrated a need for additional antivenom to stem progressive or recurrent symptoms and signs; one patient received an additional 4 vials of CROFAB. No patient in this study experienced an anaphylactic or anaphylactoid response or evidence of an early or late serum reaction as a result of administration of CROFAB.

Based on observations from the first study, the second clinical study compared two different CROFAB dosage schedules. Patients were given an initial intravenous dose of 6 vials of CROFAB with an option to retreat with an additional 6 vials, if needed, to achieve initial control of the envenomation syndrome. Initial control was defined as complete arrest of local manifestations and normalization of coagulation tests and systemic signs. Once initial control was achieved, patients were randomized to receive additional CROFAB either every 6 hours for 18 hours (Scheduled Group) or as needed (PRN Group).

In this study, CROFAB was administered to 31 patients with minimal or moderate crotalid envenomation. All 31 patients enrolled in the study achieved initial control of their envenomation with CROFAB, and 30, 25 and 26 of the 31 patients achieved a clinical response based on the ICA at 1, 6 and 12 hours respectively following initial control. Additionally, the mean ES was significantly decreased across the patient groups by the 12-hour evaluation time point (p=0.05 for the Scheduled Group; p=0.05 for the PRN Group) (see Table 6). There was no statistically significant difference between the Scheduled Group and the PRN Group with regard to the decrease in ES.

Table 6 Summary of Patient Efficacy Scores for Scheduled and PRN Groups
Time Period | Scheduled Group (n=15) Efficacy Score* Mean ± SD | PRN Group (n=16) Efficacy Score* Mean ± SD
Baseline | 4.0 ± 1.3 | 4.7 ± 2.5
End of Initial Control Antivenin Infusion(s) | 3.2 ± 1.4 | 3.3 ± 1.3
1 hour after Initial Control achieved | 3.1 ± 1.3 | 3.2 ± 0.9
6 hours after Initial Control achieved | 2.6 ± 1.5 | 2.6 ± 1.3
12 hours after Initial Control achieved | 2.4 ± 1.1** | 2.4 ± 1.2**
* No change or a decline in the Efficacy Score was considered an indication of clinical response and a sign of efficacy.
** For both the Scheduled and the PRN Groups, differences in the Efficacy Score at the four post-baseline assessment times were statistically decreased from baseline by Friedman’s test (p < 0.001)

It has been noted in published literature accounts of rattlesnake bites, that a decrease in platelets can accompany moderately severe envenomation, that was not corrected by whole blood transfusions [3]. These reductions in platelet count have been observed to last from several hours and to several days following the venomous bite [3, 4, 5]. In clinical study 2, 6 patients had pre-dosing platelet counts below 100,000/mm^3 (baseline average of 44,000/mm^3). Platelet counts for all 6 patients increased to normal levels (average 209,000/ mm^3) at 1 hour following initial control dosing with CROFAB (see Figure 1).

Figure 1 Platelet Counts from Baseline to 36 Hours for Patients with Counts <100,000/mm3 at Baseline (Clinical Study 2)

Although the difference in the decrease in ES between the two treatment groups was not significant, the data suggest that Scheduled dosing may provide better control of envenomation symptoms caused by continued leakage of venom from depot sites. Scheduled patients experienced a lower incidence of coagulation abnormalities at follow up compared with PRN patients (see Table 7) and more patients in the PRN Group showed a reduction in platelet count after discharge than in the Scheduled Group (see Figure 2). The need to administer additional CROFAB to patients in the PRN Group after initial control suggests there is continued need of antivenin for adequate treatment.

Table 7 Incidence of Recurrence of Coagulopathies at Follow-Up in Scheduled and PRN Dosing Groups
 | Scheduled Group (n=14)* (percent of patients with abnormal values)^ | PRN Group (n=16) (percent of patients with abnormal values)^
Platelet | 2/14 (14%)** | 9/16 (56%)**
Fibrinogen | 2/14 (14%) | 7/16 (44%)
^ Numbers are expressed as percent of patients that had a follow-up platelet count that was less than the count at hospital discharge, or a fibrinogen level less than 50% of the level at hospital discharge
* Follow-up data not available for one patient
** Statistically significant difference, p=0.04 by Fisher’s Exact test

Figure 2 Change in Platelet Counts in Individual Patients between Follow-Up Visits and Discharge

Patients in the Scheduled and PRN Groups are plotted separately
Only patients showing a reduced platelet count after discharge are shown

Postmarketing Retrospective Study

Following marketing approval of CROFAB, a retrospective study was conducted to assess the efficacy of CROFAB in mild, moderate and severe crotalid envenomation. This study was a multi-center, retrospective chart review of medical records of snakebite patients treated with CROFAB that compared treatment and outcomes of severe envenomation with those of mild and moderate envenomation. The primary efficacy variable was severity of envenomation as determined by a 7-point severity score. Patients were classified as having mild, moderate or severe envenomation based on their scores just prior to receiving antivenom. Those subjects with a severity score of 5 or 6 at the start of antivenom therapy were a priori defined as severe envenomations; those with a score of 3 or 4 were defined as moderate envenomations; and those with a score of 1 or 2 were defined as mild envenomations (see Table 5). A total of 247 patients of all severities were included in the study. Patients with enough data to determine baseline severity were included in the efficacy evaluation. This comprised a cohort of 209 patients, of whom 28 were classified as severe.

Improvement in severity score was observed in all 28 severely envenomated patients. Improvement was noted for each severe venom effect studied, including limb pain and swelling; cardiovascular, respiratory, gastrointestinal and neurologic effects; and coagulopathy/defibrination syndrome, thrombocytopenia and significant/spontaneous bleeding. The median dose of CROFAB administered to treat these severe venom effects was 9 vials (median of 2 doses). Initial control of envenomation was achieved in 57% (16/28) of severely envenomated patients and 87% (158/181) of mild/moderate envenomated patients. In both groups, failure to achieve initial control was most commonly attributable to persistent coagulopathy and/or thrombocytopenia, which occurred in 1 severe case. All 12 severe patients who did not achieve initial control received only one bolus dose of 4 to 6 vials to try to achieve initial control of envenomation. Of the 23 mild/moderate cases who did not achieve initial control, 19 did not follow recommended dosing for number of doses and vials. Whether initial control could have been achieved with larger initial doses of antivenom cannot be determined from this retrospective study. All patients, whether or not they achieved initial control, experienced significant improvement of venom effects and decreased severity scores after receiving CROFAB. Among patients with severe envenomation who did not achieve initial control, median severity score improved from 5 (range: 5 – 6) before CROFAB administration to 2 (range: 1 – 4) at the last loading dose. No patient in this analysis had a severity score greater than 3 at time of final clinical assessment.

15 REFERENCES

1. Consroe P, Egen NB, Russell FE, Gerrish K, Smith DC, Sidki A, et al. Comparison of a new ovine antigen binding fragment (Fab) antivenin for United States Crotalidae with the commercial antivenin for protection against venom induced lethality in mice. J Trop Med Hyg 1995; 53(5):507 510.
2. Dart RC, Hurlbut KM, Garcia R, Boren J. Validation of a severity score for the assessment of Crotalid snakebite. Ann Emerg Med 1996; 27(3):321 326.
3. Lavonas EJ, Ruha AM, Banner W, Bebarta V, Bernstein JN, Bush SP, Kerns WP, Richardson WH, Seifert SA, Tanen DA, Curry SC, Dart RC. Unified treatment algorithm for the management of crotaline snakebite in the United States: results of an evidence-informed consensus workshop. BMC Emerg Med February 3 2011;11:2 (http://www.biomedcentral.com/1471-227X/11/2).
4. La Grange RG and Russell FE. Blood platelet studies in man and rabbits following Crotalus envenomation. Proc West Pharmacol Soc 1970;13:99-105.
5. Lyons WJ. Profound thrombocytopenia associated with Crotalus ruber ruber envenomation: a clinical case. Toxicon 1971; 9:237 240.
6. Tallon RW, Koch KL, Barnes SG, Ballard JO. Letter to Editor. N Engl J Med 1981;305:1347.
7. Quarre JP, Lecomte J, Lauwers D, Gilbert P, Thiriaux J. Allergy to latex and papain. J Allergy Clin Immunol 1995; 95(4):922.
8. Baur X, Chen Z, Rozynek P, Düser D, Raulf Heimsoth M. Cross reacting IgE antibodies recognizing latex allergens, including Hev b 1, as well as papain. Allergy 1995; 50(7):604 609.
9. Furlow TG, Brennan LV. Purpura following timber rattlesnake (Crotalus horridus horridus) envenomation. Cutis 1985; 35:234 236.
10. Budzynski AZ, Pandya BV, Rubin RN, Brizuela BS, Soszka T, Stewart GJ. Fibrinogenolytic afibrinogenemia after envenomation by western diamondback rattlesnake (Crotalus atrox). Blood 1984; 63(1):1 14.
11. Kojis FG. Serum sickness and anaphylaxis. Am J Dis Child 1997;93 350.
12. Kirkpatrick CH, The Digibind Study Advisory Panel. Allergic histories and reactions of patients treated with digoxin immune Fab (ovine) antibody. Am J Emerg Med 1991; 9(2 Suppl 1):7 10.
13. Lavonas EJ, Khatri V, Daugherty C, Bucher-Bartelson B, King T, Dart RC. Medically significant late bleeding after treated Crotaline envenomation: A systematic review. Ann Emerg Med 2014;63(1):71-78.
14. Pizon AF, Riley BD, LoVecchio F, and Gill R. Safety and Efficacy of Crotalidae Polyvalent Immune Fab in Pediatric Crotaline Envenomations. Acad Emerg Med 2007;14:373-376.
15. Offerman SR, Bush SP, Moynihan JA, Clark RF. Crotaline Fab Antivenom for the Treatment of Children with Rattlesnake Envenomation. Pediatrics 2002; 110(5):968-971.

16 HOW SUPPLIED/STORAGE AND HANDLING

How Supplied

CROFAB is supplied as a carton that contains 2 vials of product (diluent not included) [NDC 50633-110-12]. Each vial of CROFAB contains up to 1 gram of lyophilized total protein and not less than the indicated number of mouse LD50 neutralizing units:

Snake Species Used for Antivenin Component | Minimum mouse LD50 Units per vial
C. atrox (Western Diamondback rattlesnake) | 1270
C. adamanteus (Eastern Diamondback rattlesnake) | 420
C. scutulatus (Mojave rattlesnake) | 5570
A. piscivorus (Cottonmouth or Water Moccasin) | 780

Storage and Handling

- Store vials at 2° to 8°C (36° to 46°F). A temperature excursion for no longer than 7 days within the range of -20° to 25°C (-4° to 77°F) is permitted.
- Do not freeze.
- Use within 4 hours after reconstitution.

17 PATIENT COUNSELING INFORMATION

- Advise patients to contact their physician immediately if they experience unusual bruising or bleeding (e.g., nosebleeds, excessive bleeding after brushing teeth, the appearance of blood in stools or urine, excessive menstrual bleeding, petechiae, excessive bruising or persistent oozing from superficial injuries) after hospital discharge.Such bruising or bleeding may occur for up to 1 week or longer following initial treatment.
- Advise patients to contact their physician immediately if they experience any signs and symptoms of delayed allergic reactions or serum sickness (e.g., rash, pruritus, urticaria) after hospital discharge.

Manufactured for
and distributed by:

BTG International Inc.
West Conshohocken, PA 19428

U.S. License No. 1861

CroFab® is a registered trademark of BTG International Inc.
BTG and the BTG roundel logo are registered trademarks of BTG International Ltd.

P11012F